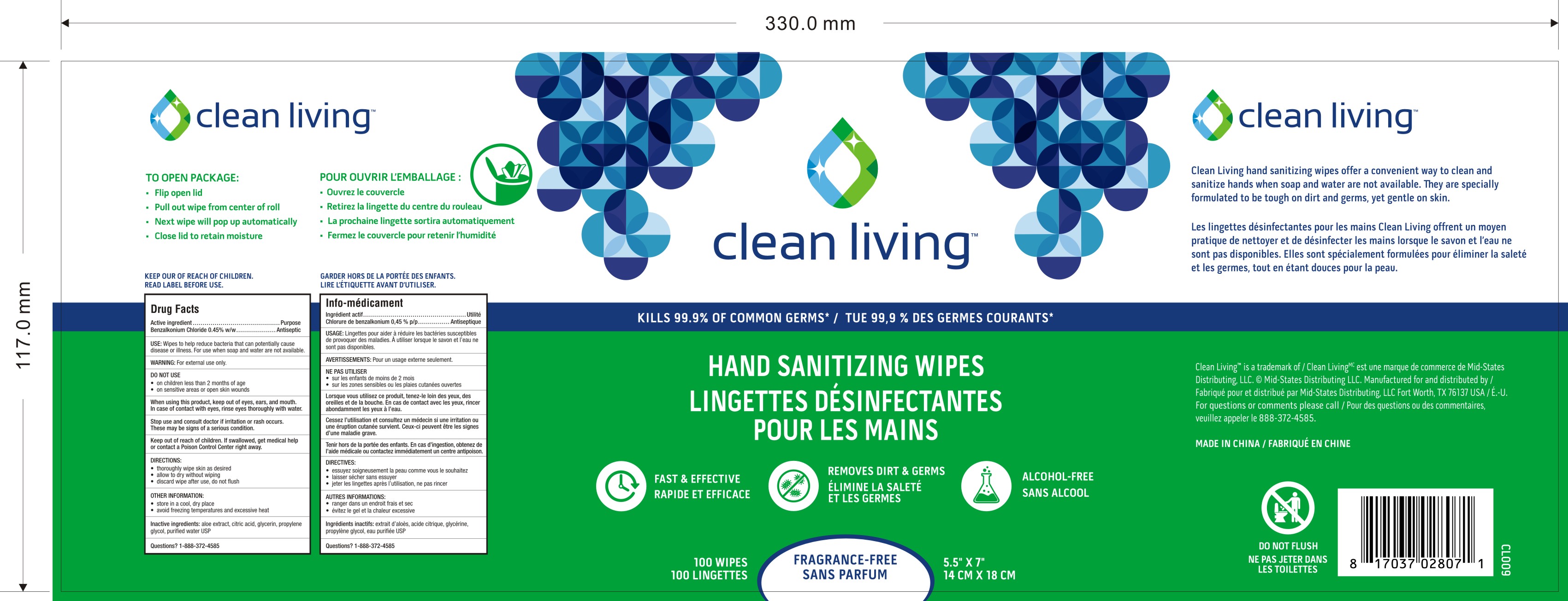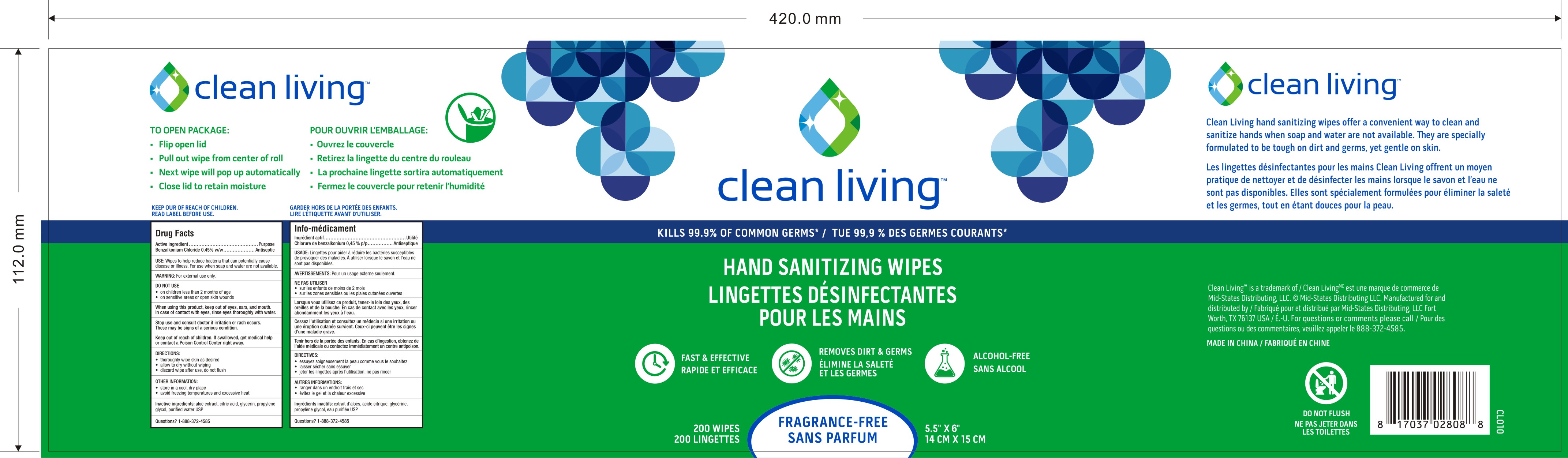 DRUG LABEL: HAND SANITIZING WIPES
NDC: 81329-5667 | Form: CLOTH
Manufacturer: Mid-States Distributing, LLC
Category: otc | Type: HUMAN OTC DRUG LABEL
Date: 20211208

ACTIVE INGREDIENTS: BENZALKONIUM CHLORIDE 0.45 g/100 g
INACTIVE INGREDIENTS: ALOE; ANHYDROUS CITRIC ACID; GLYCERIN; PROPYLENE GLYCOL; WATER

Active Ingredient(s)

Benzalkonium Chloride 0.45% w/w. Purpose: Antiseptic

Purpose

Antiseptic, Hand Sanitizer

Use

Wipes to help reduce bacteria that can potentially cause disease or illness. For use when soap and water are not available.

Warnings

For external use only.

Do not use

- on children less than 2 months of age
- on sensitive areas or open skin wounds

When using this product keep out of eyes, ears, and mouth. In case of contact with eyes, rinse eyes thoroughly with water.
Stop use and ask a doctor if irritation or rash occurs. These may be signs of a serious condition.
Keep out of reach of children. If swallowed, get medical help or contact a Poison Control Center right away.

Stop use and consult doctor if irritation or rash occurs. These may be signs of a serious condition.

Keep out of reach of children. If swallowed, get medical help or contact a Poison Control Center right away.

Directions

- thoroughly wipe skin as desired.
- allow to dry without wiping.
- discard wipe after use, do not flush.

Other information

- Store in a cool, dry place.
- Avoid freezing temperatures and excessive heat

Inactive ingredients

aloe extract, citric acid, glycerin, propylene glycol, purified water USP.

Package Label - Principal Display Panel

100 Wipes in 1 Canister NDC: 81329-5667-1

Package Label - Principal Display Panel

200 Wipes in 1 Canister NDC: 81329-5667-2